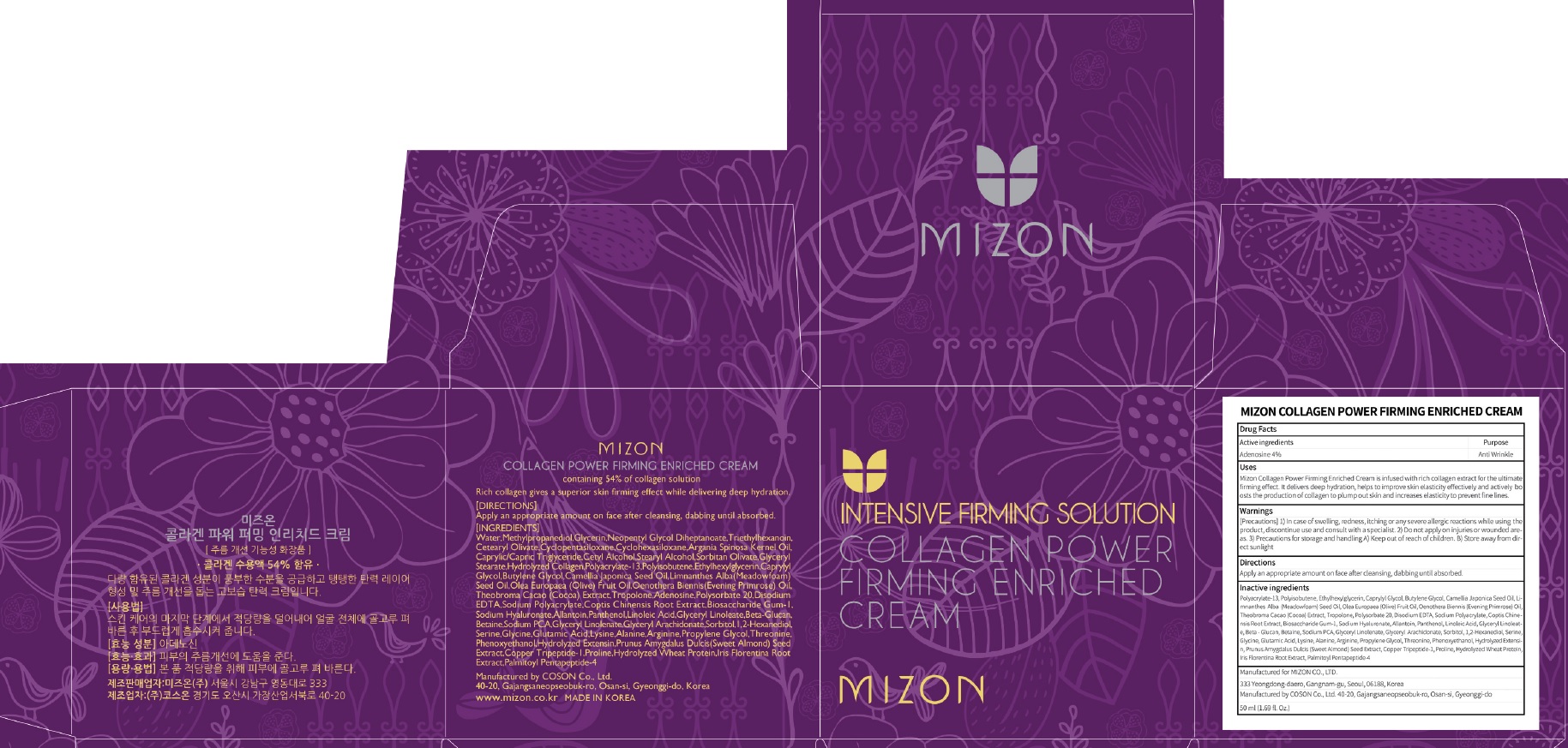 DRUG LABEL: MIZON COLLAGEN POWER FIRMING ENRICHED CREA M
NDC: 57718-280 | Form: CREAM
Manufacturer: MIZON CO.,LTD.
Category: otc | Type: HUMAN OTC DRUG LABEL
Date: 20180724

ACTIVE INGREDIENTS: Adenosine 0.02 g/50 mL
INACTIVE INGREDIENTS: Ethylhexylglycerin; Caprylyl Glycol

ACTIVE INGREDIENT

Active ingredients: Adenosine 0.04%

INACTIVE INGREDIENT

Inactive ingredients:

Polyacrylate-13, Polyisobutene, Ethylhexylglycerin, Caprylyl Glycol, Butylene Glycol, Camellia Japonica Seed Oil, Limnanthes Alba (Meadowfoam) Seed Oil, Olea Europaea (Olive) Fruit Oil, Oenothera Biennis (Evening Primrose) Oil, Theobroma Cacao (Cocoa) Extract, Tropolone, Polysorbate 20, Disodium EDTA, Sodium Polyacrylate, Coptis Chinensis Root Extract, Biosaccharide Gum-1, Sodium Hyaluronate, Allantoin, Panthenol, Linoleic Acid, Glyceryl Linoleate, Beta-Glucan, Betaine, Sodium PCA, Glyceryl Linolenate, Glyceryl Arachidonate, Sorbitol, 1,2-Hexanediol, Serine, Glycine, Glutamic Acid, Lysine, Alanine, Arginine, Propylene Glycol, Threonine, Phenoxyethanol, Hydrolyzed Extensin, Prunus Amygdalus Dulcis (Sweet Almond) Seed Extract, Copper Tripeptide-1, Proline, Hydrolyzed Wheat Protein, Iris Florentina Root Extract, Palmitoyl Pentapeptide-4

PURPOSE

Purpose: Anti Wrinkle

WARNINGS

[Precautions]

1) In case of swelling, redness, itching or any severe allergic reactions while using the product, discontinue use and consult with a specialist. 2) Do not apply on injuries or wounded areas. 3) Precautions for storage and handling A) Keep out of reach of children. B) Store away from direct sunlight

KEEP OUT OF REACH OF CHILDREN

Uses

Mizon Collagen Power Firming Enriched Cream is infused with rich collagen extract for the ultimate firming effect. It delivers deep hydration, helps to improve skin elasticity effectively and actively boosts the production of collagen to plump out skin and increases elasticity to prevent fine lines.

Directions

Apply an appropriate amount on face after cleansing, dabbing until absorbed.